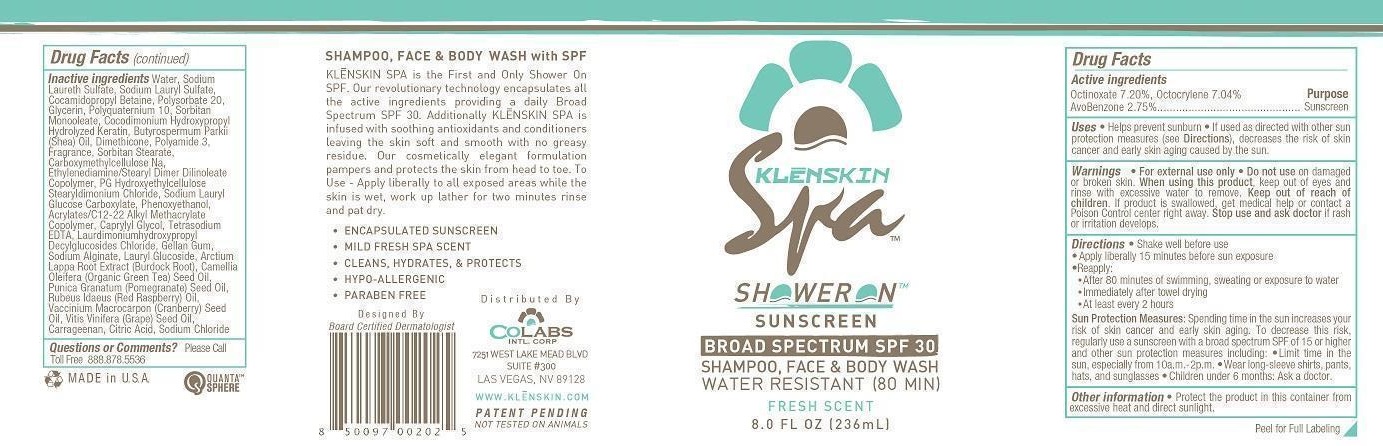 DRUG LABEL: KLENSKIN SHOWERON SUNSCREEN SPA
NDC: 61369-103 | Form: GEL
Manufacturer: CoLabs Intl. Corp
Category: otc | Type: HUMAN OTC DRUG LABEL
Date: 20240115

ACTIVE INGREDIENTS: AVOBENZONE 2.75 g/100 mL; OCTOCRYLENE 7.04 g/100 mL; OCTINOXATE 7.2 g/100 mL
INACTIVE INGREDIENTS: WATER; SODIUM LAURETH SULFATE; SODIUM LAURYL SULFATE; COCAMIDOPROPYL BETAINE; POLYSORBATE 20; GLYCERIN; POLYQUATERNIUM-10 (125 MPA.S AT 2%); SORBITAN MONOOLEATE; HYDROLYZED ELASTIN, BOVINE, ALKALINE (1000 MW); SHEANUT OIL; DIMETHICONE; POLYACRYLAMIDE (1500 MW); SORBITAN MONOSTEARATE; CARBOXYMETHYLCELLULOSE SODIUM; ETHYLENEDIAMINE; DIISOSTEARYL DIMER DILINOLEATE; HYDROXYETHYL CELLULOSE (100 MPA.S AT 2%); DISTEARYLDIMONIUM CHLORIDE; SODIUM LAURYL GLYCOL CARBOXYLATE; PHENOXYETHANOL; CARBOMER COPOLYMER TYPE A; CAPRYLYL GLYCOL; EDETATE SODIUM; HYDROXYETHYL LAURDIMONIUM CHLORIDE; GELLAN GUM (LOW ACYL); SODIUM ALGINATE; LAURYL GLUCOSIDE; ARCTIUM LAPPA ROOT; CAMELLIA OLEIFERA SEED; POMEGRANATE SEED OIL; RASPBERRY SEED OIL; CRANBERRY SEED OIL; GRAPE SEED OIL; CARRAGEENAN; ANHYDROUS CITRIC ACID; SODIUM CHLORIDE

COLABS - KLENSKIN SHOWERON SUNSCREEN SPA SPF 30 (61369-103)

ACTIVE INGREDIENTS

AVOBENZONE 2.75%

OCTOCRYLENE 7.04%

OCTINOXATE 7.2%

PURPOSE

SUNSCREEN

USES

- HELPS PREVENT SUNBURN
- IF USED AS DIRECTED WITH OTHER SUN PROTECTION MEASURES (SEE DIRECTIONS), DECREASES THE RISK OF SKIN CANCER AND EARLY SKIN AGING CAUSED BY THE SUN.

WARNINGS

- FOR EXTERNAL USE ONLY
- DO NOT USE ON DAMAGED OR BROKEN SKIN.
- WHEN USING THIS PRODUCT, KEEP OUT OF EYES AND RINSE WITH EXCESSIVE WATER TO REMOVE.

KEEP OUT OF REACH OF CHILDREN. IF PRODUCT IS SWALLOWED, GET MEDICAL HELP OR CONTACT A POISON CONTROL CENTER RIGHT AWAY.

STOP USE AND ASK A DOCTOR IF RASH OR IRRITATION DEVELOPS.

DIRECTIONS

- SHAKE WELL BEFORE USE
- APPLY LIBERALLY 15 MINUTES BEFORE SUN EXPOSURE
- REAPPLY:
- AFTER 80 MINUTES OF SWIMMING, SWEATING OR EXPOSURE TO WATER
- IMMEDIATELY AFTER TOWEL DRYING
- AT LEAST EVERY 2 HOURS

OTHER SAFETY INFORMATION

SUN PROTECTION MEASURES: SPENDING TIME IN THE SUN INCREASES YOUR RISK OF SKIN CANCER AND EARLY SKIN AGING. TO DECREASE THIS RISK, REGULARLY USE A SUNSCREEN WITH A BROAD SPECTRUM SPF OF 15 OR HIGHER AND OTHER SUN PROTECTION MEASURES INCLUDING:

- LIMIT TIME IN THE SUN, ESPECIALLY FROM 10 A.M. - 2 P.M.
- WEAR LONG-SLEEVED SHIRTS, PANTS, HATS, AND SUNGLASSES
- CHILDREN UNDER 6 MONTHS: ASK A DOCTOR.

OTHER INFORMATION

- PROTECT THE PRODUCT IN THIS CONTAINER FROM EXCESSIVE HEAT AND DIRECT SUNLIGHT.

INACTIVE INGREDIENTS

WATER, SODIUM LAURETH SULFATE, SODIUM LAURYL SULFATE, COCAMIDOPROPYL BETAINE, POLYSORBATE 20, GLYCERIN, POLYQUATERNIUM-10, SORBITAN MONOOLEATE, COCODIMONIUM HYDROXYPROPYL HYDROLYZED KERATIN, BUTYROSPERMUM PARKII (SHEA) OIL, DIMETHICONE, POLYAMIDE-3, FRAGRANCE, SORBITAN STEARATE, CARBOXYMETHYCELLULOSE NA, ETHYLENEDIAMINE/STEARYL DIMER DILINOLEATE COPOLYMER, PG HYDROXYETHYLCELLULOSE STEARDIMONIUM CHLORIDE, SODIUM LAURYL GLUCOSE CARBOXYLATE, PHENOXYETHANOL, ACRYLATES/C12-22 ALKYL METHACRYLATE COPOLYMER, CAPRYLYL GLYCOL, TETRASODIUM EDTA, LAURYLDIMONIUMHYDROXYPROPYL DECYLGLUCOSIDES CLORIDE, GELLAN GUM, SODIUM ALGINATE, LAURYL GLUCOSIDE, ARCTIUM LAPPA (BURDOCK ROOT) EXTRACT, CAMELIA OLEIFERA (GREEN TEA) SEED OIL, PUNICA GRANATUM (POMEGRANATE) SEED OIL, RUBEUS IDAEUS (RED RASPBERRY) OIL, VACCINIUM MACROCARPON (CRANBERRY) SEED OIL, VITIS VINIFERA (GRAPE) SEED OIL, CARRAGEENAN, CITRIC ACID, SODIUM CHLORIDE

QUESTIONS OR COMMENTS? PLEASE CALL TOLL FREE 888.878.5536